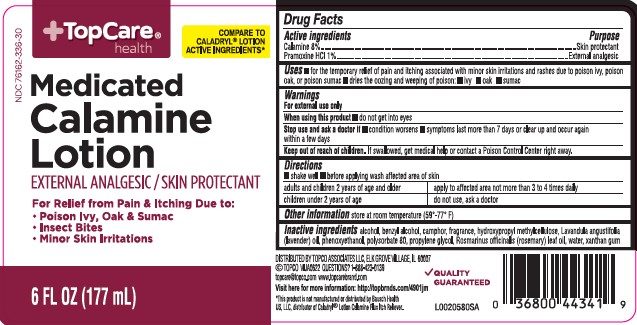 DRUG LABEL: Calamine
NDC: 76162-336 | Form: LOTION
Manufacturer: Topco Associates LLC
Category: otc | Type: HUMAN OTC DRUG LABEL
Date: 20260213

ACTIVE INGREDIENTS: FERRIC OXIDE RED 80 mg/1 mL; PRAMOXINE HYDROCHLORIDE 10 mg/1 mL
INACTIVE INGREDIENTS: BENZYL ALCOHOL; ALCOHOL; CAMPHOR (NATURAL); HYPROMELLOSE, UNSPECIFIED; LAVENDER OIL; PHENOXYETHANOL; POLYSORBATE 80; PROPYLENE GLYCOL; ROSEMARY OIL; WATER; XANTHAN GUM

Top Care 336.003/336AG
Medicated Calamine Lotion

Active ingredients

Calamine 8%

Pramoxine HCl 1%

Purpose

Skin protectant

External analgesic

Use

- for the temporary relief of pain and itching associated with minot skin irritations and rashes due to poison ivy, poison oak, or poison sumac
- dries the oozing and weeping of poison:
- ivy
- oak
- sumac

Warnings

For external use only

When using this product

- do not get into eyes

Stop use and ask a doctor

- condition worsens
- symptoms last more than 7 days or clean up and occur again within a few days

Keep out of reach of children.

If swallowed, get medical help or contact a Poison Control Center right away.

Directions

- shake well
- before applying was affected are of skin

Adults and children 2 years of age and older - apply to affected area not more than 3 to 4 times daily

Children under 2 years of age - do not use, ask a doctor

Other information

store at room temperature (59°-77°F)

Inactive ingredients

alcohol, benzyl alcohol, camphor, fragrance, hydroxypropyl methylcellulose, Lavandula angustifolia (lavender) oil, phenoxyethanol, polysorbate 80, propylene glycol, Rosmarinus officinalis (rosemary) leaf oil, water, xanthan gum

ADVERSE REACTION

DISTRIBUTED BY TOPCO ASSOCIATES LLC,

ELK GROVE VILLAGE, IL 60007

©TOPCO VIJA0622 QUESTIONS? 1-888-423-0139

topcare@topco.com www.topcarebrand.com

Quality Guaranteed

Visit here for more information: http://topbrnds.com/4901jm

Disclaimer

*This product is not manufactured or distributed by Bausch Health US, LLC, distributer of CaladrylLotion Calamine Plus Itch Reliever

principal display panel

TopCare®Health

COMPARE TO CALADRYL®LOTION ACTIVE INGREDIENTS*

NDC 76162-336-30

MEDICATED

Calamine Lotion

EXTERANAL ANALGESIC/SKIN PROTECTANT

For Relief from Pain & Itching Due to:

- Poison Ivy, Oak & Sumac
- Insect Bites
- Minor Skin Irritations

6 FL OZ (177 mL)